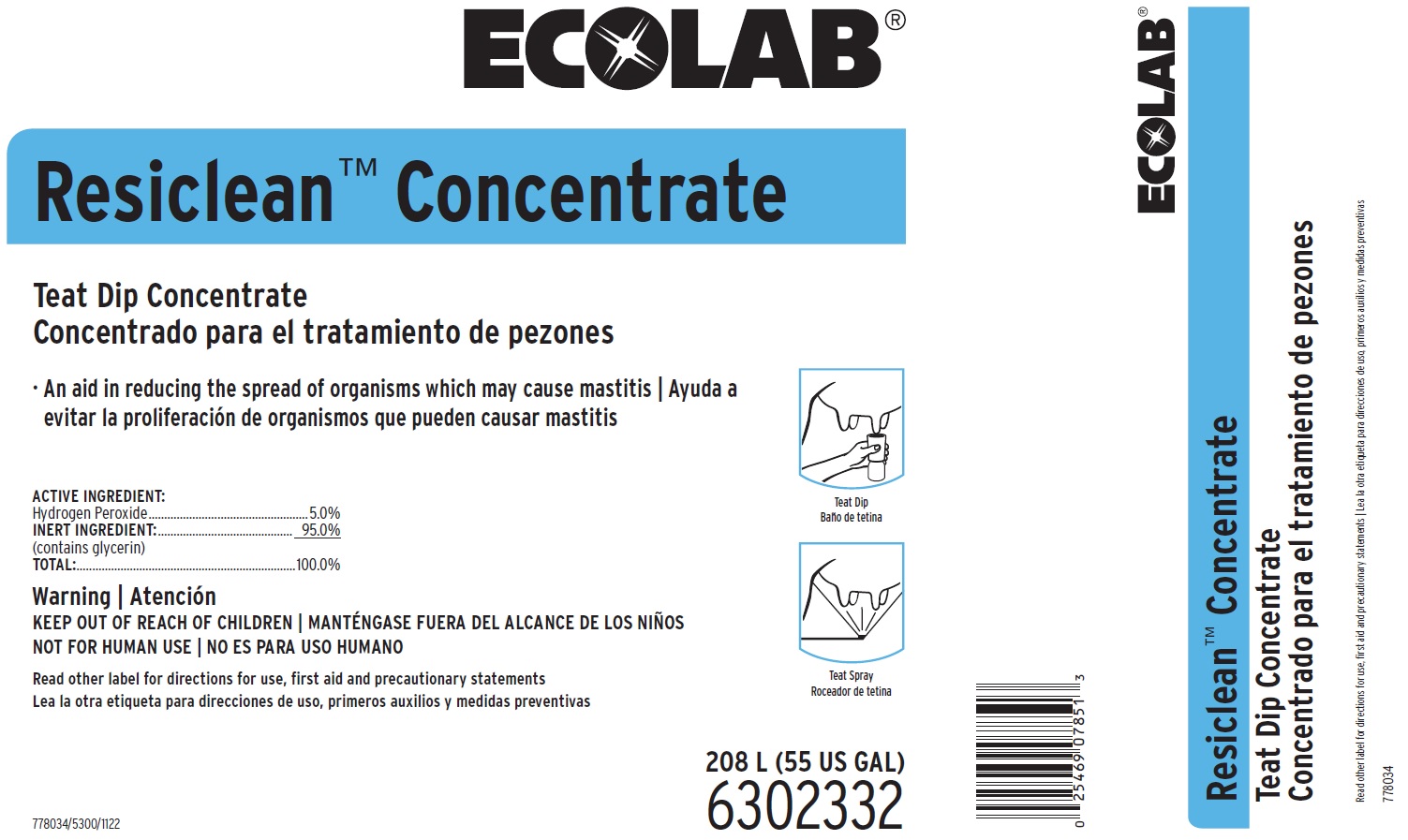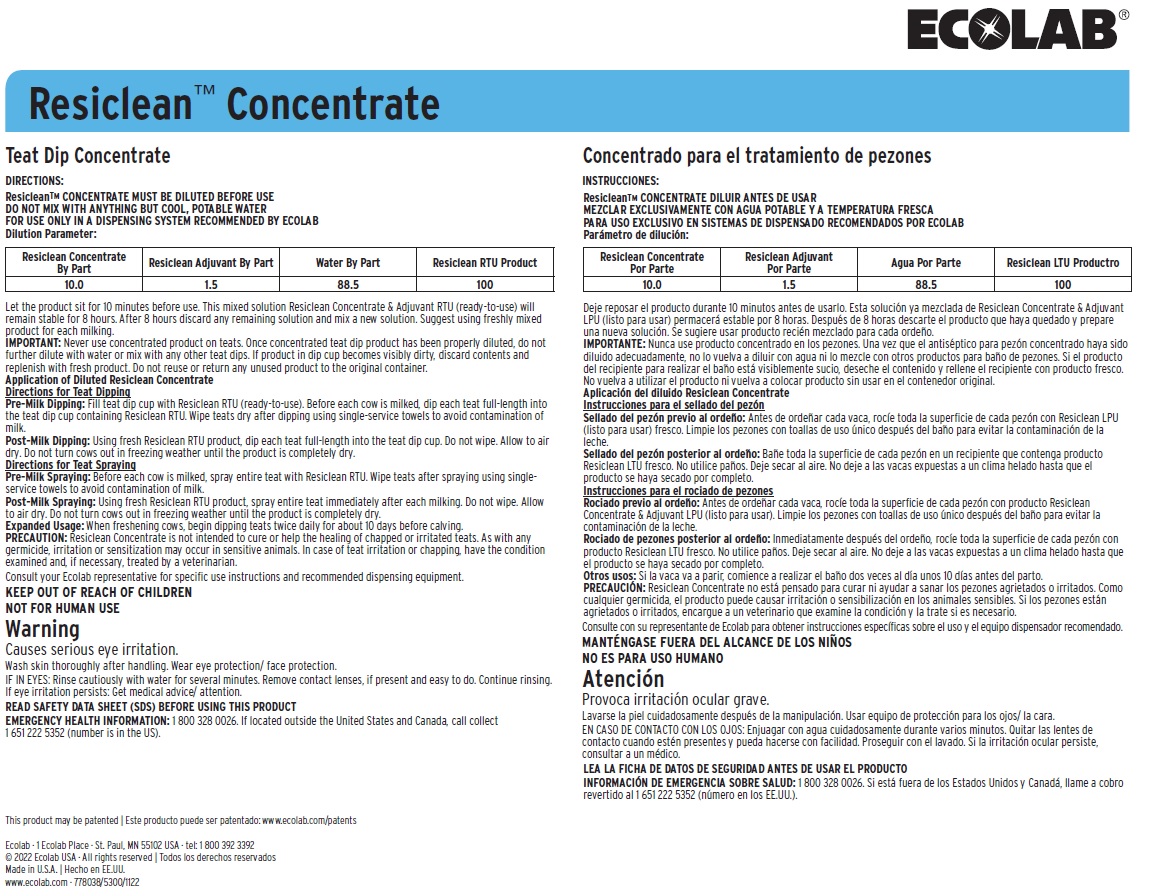 DRUG LABEL: Resiclean Concentrate
NDC: 47593-647 | Form: SOLUTION
Manufacturer: Ecolab Inc.
Category: animal | Type: OTC ANIMAL DRUG LABEL
Date: 20250722

ACTIVE INGREDIENTS: HYDROGEN PEROXIDE 50 mg/1 mL
INACTIVE INGREDIENTS: WATER; GLYCERIN

KEEP OUT OF REACH OF CHILDREN

NOT FOR HUMAN USE

Warning

Causes serious eye irritation.

Wash skin thoroughly after handling. Wear eye protection/ face protection.

DIRECTIONS:

ResicleanTM CONCENTRATE

MUST BE DILUTED BEFORE USE

DO NOT MIX WITH ANYTHING BUT COOL, POTABLE WATER

FOR USE ONLY IN A DISPENSING SYSTEM RECOMMENDED BY ECOLAB

Dilution Parameter:

Resiclean Concentrate By Part | Resiclean Adjuvant By Part | Water By Part | Resiclean RTU Product
10.0 | 1.5 | 88.5 | 100

Let the product sit for 10 minutes before use. This mixed solution Resiclean Concentrate & Adjuvant RTU (ready-to-use) will remain stable for 8 hours. After 8 hours discard any remaining solution and mix a new solution. Suggest using freshly mixed product for each milking.

IMPORTANT: Never use concentrated product on teats. Once concentrated teat dip product has been properly diluted, do not further dilute with water or mix with any other teat dips. If product in dip cup becomes visibly dirty, discard contents and replenish with fresh product. Do not reuse or return any unused product to the original container.

Application of Diluted Resiclean Concentrate

Directions for Teat Dipping

Pre-Milk Dipping: Fill teat dip cup with Resiclean RTU (ready-to-use). Before each cow is milked, dip each teat full-length into the teat dip cup containing Resiclean RTU. Wipe teats dry after dipping using single-service towels to avoid contamination of milk.

Post-Milk Dipping: Using fresh Resiclean RTU product, dip each teat full-length into the teat dip cup. Do not wipe. Allow to air dry. Do not turn cows out in freezing weather until the product is completely dry.

Directions for Teat Spraying

Pre-Milk Spraying: Before each cow is milked, spray entire teat with Resiclean RTU. Wipe teats after spraying using single-service towels to avoid contamination of milk.

Post-Milk Spraying: Using fresh Resiclean RTU product, spray entire teat immediately after each milking. Do not wipe. Allow to air dry. Do not turn cows out in freezing weather until the product is completely dry.

Expanded Usage: When freshening cows, begin dipping teats twice daily for about 10 days before calving.

PRECAUTION: Resiclean Concentrate is not intended to cure or help the healing of chapped or irritated teats. As with any germicide, irritation or sensitization may occur in sensitive animals. In case of teat irritation or chapping, have the condition examined and, if necessary, treated by a veterinarian.

Consult your Ecolab representative for specific use instructions and recommended dispensing equipment.

OTHER SAFETY INFORMATION

IF IN EYES: Rinse cautiously with water for several minutes. Remove contact lenses, if present and easy to do. Continue rinsing. If eye irritation persists: Get medical advice/ attention.

READ SAFETY DATA SHEET (SDS) BEFORE USING THIS PRODUCT

EMERGENCY HEALTH INFORMATION: 1 800 328 0026. If located outside the United States and Canada, call collect 1 651 222 5352 (number is in the US).

Principal display panel and representative label

ECOLAB

Resiclean™ Concentrate

Teat Dip Concentrate

An aid in reducing the spread of organisms which may cause mastitis

ACTIVE INGREDIENT:

Hydrogen Peroxide....................................................5.0%

INERT INGREDIENT:............................................ 95.0%

(contains glycerin)

TOTAL:......................................................................100.0%

Warning

KEEP OUT OF REACH OF CHILDREN

NOT FOR HUMAN USE

This product may be patented www.ecolab.com/patents

Ecolab · 1 Ecolab Place · St. Paul, MN 55102 USA · tel: 1 800 392 3392

© 2022 Ecolab USA · All rights reserved

Made in U.S.A.

www.ecolab.com · 778038/5300/1122